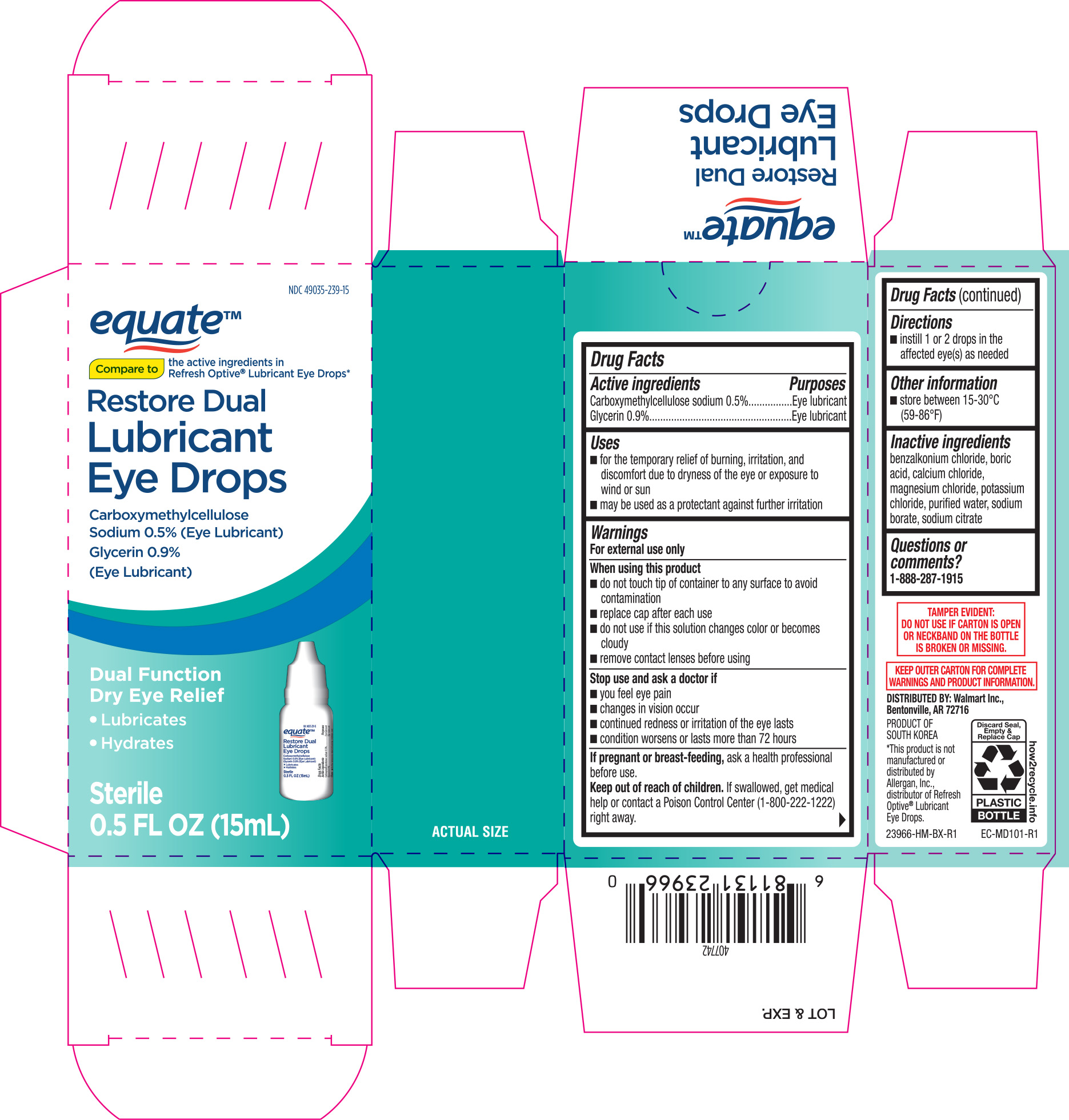 DRUG LABEL: Equate Restore Dual Lubricating
NDC: 49035-239 | Form: SOLUTION/ DROPS
Manufacturer: Walmart
Category: otc | Type: HUMAN OTC DRUG LABEL
Date: 20180320

ACTIVE INGREDIENTS: CARBOXYMETHYLCELLULOSE SODIUM 5 mg/1 mL; GLYCERIN 9 mg/1 mL
INACTIVE INGREDIENTS: BORIC ACID; SODIUM CITRATE; CALCIUM CHLORIDE; POTASSIUM CHLORIDE; WATER; SODIUM BORATE; MAGNESIUM CHLORIDE; BENZALKONIUM CHLORIDE

Equate NBE Refresh Optive 0.5 oz

Active ingredients Purpose

Caboxymethylcellulose sodium 0.5%..................Eye lubricant

Glycerin 0.9%......................................................Eye lubricant

Uses

- for the temporary relief of burning, irritation, and discomfort due to dryness of the eye or exposure to wind or sun
- may be used as a protectant against further irritation

Warnings

For external use only

When using this product

- do not touch tip of container to any surface to avoid contamination
- replace cap after each use
- do not use if this solution changes color or becomes cloudy
- remove contact lenses before using

Stop use and ask a doctor if

- you feel eye pain
- changes in vision occur
- continued redness or irritation of the eyes lasts
- condition worsens or lasts more than 72 hours

PREGNANCY OR BREAST FEEDING

If pregnant or breast-feeding, ask a health professional before use.

Keep out of reach of children. If swallowed, get medical help or contact a Poison Control Center (1-800-222-1222) right away.

Directions

- instill 1 or 2 drops in the affected eye(s) as needed
- store between 15-30°C (59-86°F)

Inactive ingredients

benzalkonium chloride, boric acid, calcium chloride, magnesium chloride, potassium chloride, purifed water, sodium borate, sodium citrate

DOSAGE AND ADMINISTRATION

Distributed by:

Wal-Mart Stores, Inc.

Bentonville, AR 72716

Made in South Korea